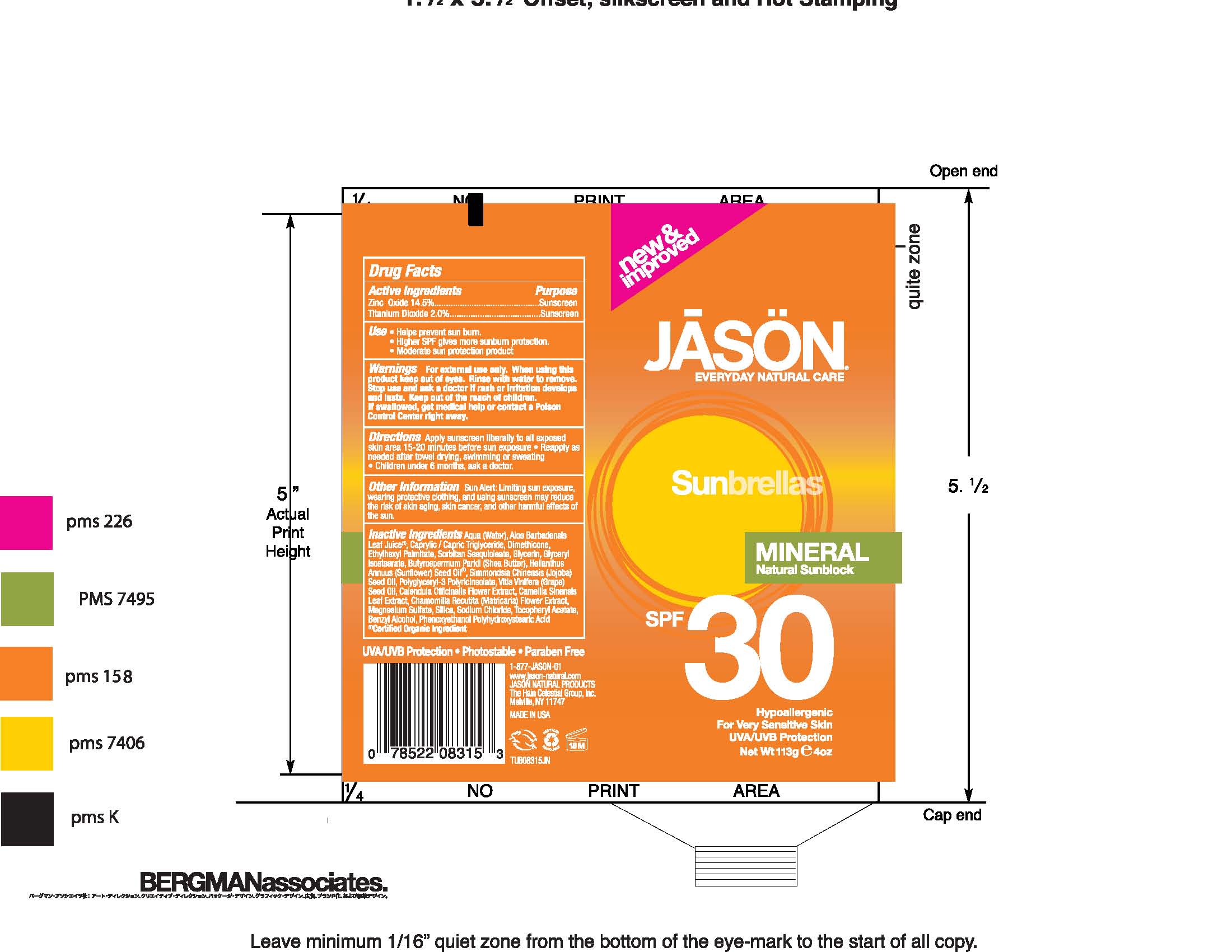 DRUG LABEL: Sunbrellas Mineral Sunblock SPF 30
NDC: 61995-0210 | Form: CREAM
Manufacturer: The Hain Celestial Group, Inc.
Category: otc | Type: HUMAN OTC DRUG LABEL
Date: 20100810

ACTIVE INGREDIENTS: Zinc Oxide 14.5 g/100 g; Titanium Dioxide 2.0 g/100 g

Drug Facts

ACTIVE INGREDIENTS

Zinc Oxide 14.5.0%
Titanium Dioxide 2.0%

USES

- Helps prevent sunburns
- Higher SPF gives more sunburn protection
- Moderate sun protection product
- apply sunscreen liberally to all exposed skin area 15 to 20 minutes before sun exposure
- Reapply as needed after towel drying, swimming or sweating
- Children after 6 months, ask doctor

WARNINGS

For external use only. When using this product keep out of eyes. Rinse with water to remove. Stop use and ask a doctor if rash or irritation develops and lasts. Keep out of reach of children. If swallowed, get medical help or contact Poison Center right away.

OTHER INFORMATION

Sun Alert: Limiting sun exposure, wearing protective clothing, and using sunscreen may reduce the risk of skin aging, skin cancer and other harmful effects of the sun.

QUESTIONS?

1-877-JASON-01

www.jason-natural.com

The Hain Celestial Group, Inc.

Melville, NY 11747

Made in U.S.A.